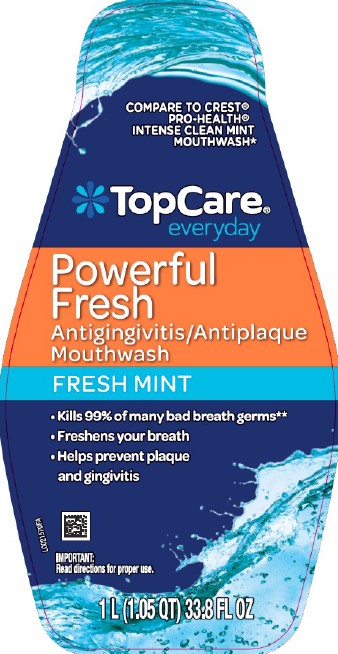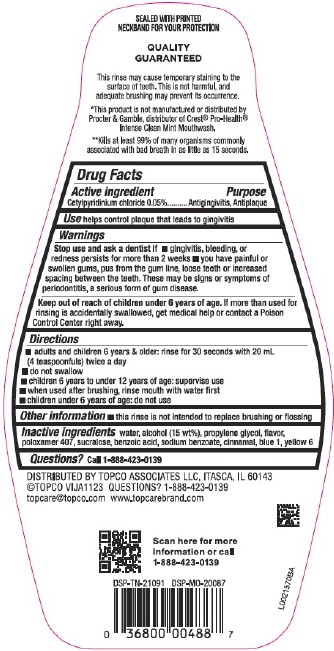 DRUG LABEL: Antigingivitis/Antiplaque
NDC: 76162-953 | Form: MOUTHWASH
Manufacturer: Topco Associates LLC
Category: otc | Type: HUMAN OTC DRUG LABEL
Date: 20260213

ACTIVE INGREDIENTS: CETYLPYRIDINIUM CHLORIDE 0.5 mg/1 mL
INACTIVE INGREDIENTS: WATER; ALCOHOL; PROPYLENE GLYCOL; POLOXAMER 407; SUCRALOSE; BENZOIC ACID; SODIUM BENZOATE; CINNAMALDEHYDE; FD&C BLUE NO. 1; FD&C YELLOW NO. 6

Top Care D53.000/D53AA-AB
Powerful Fresh Mint Mouthwash

Tamper Evident Statement

SEALED WITH PRINTED NECKBAND FOR YOUR PROTECTION

Claims & Disclaimer

QUALITY GUARANTEED

This rinse may cause temporary staining to the surface of teeth. This is not harmful, and adequate brushing may prevent its occurrence.

*This product is not manufactured or distributed by Procter & Gamble, distributor of Crest® Pro-Health® Intense Clean Mint Mouthwash.

**Kills at least 99% of many organisms commonly associated with bad breath in as little as 15 seconds.

Active Ingredient

Cetylpyridinium Chloride 0.05%

Purpose

Antigingivitis, Antiplaque

Use

helps control plaque that leads to gingivitis

Warnings

for this product

Stop use and ask a dentist if

- gingivitis, bleeding, or redness persists for more than 2 weeks
- you have painful or swollen gums, pus from the gum line, loose teeth or increased spacing between the teeth. These may be signs or symptoms of periodontitis, a serious form of gum disease.

Keep out of reach of children under 6 years of age.

If more than used for rinsing is accidentally swallowed, get medical help or contact a Poison Control Center right away.

Directions

- adults and children 6 years & older: rinse for 30 seconds with 20 mL (4 teaspoonfuls) twice a day
- do not swallow
- children 6 years to under 12 years of age: supervise use
- when used after brushing, rinse mouth with water first
- children under 6 years of age: do not use

Other information

- this rinse is not intended to replace brushing or flossing

Inactive ingredients

water, alcohol (15 wt%), propylene glycol, flavor, poloxamer 407, sucralose, benzoic acid, sodium benzoate, cinnamal, blue 1, yellow 6

Questions?

Call 1-888-423-0139

Adverse reaction

DISTRIBUTED BY TOPCO ASSOCIATES LLC, ITASCA, IL 60143

©TOPCO VIJA1123 QUESTIONS? 1-888-423-0139

topcare@topco.com www.topcarebrand.com

Scan here for more information or call 1-888-423-0139

DSP-TN-21091 DSP-MO-20087

Principal Panel Display

COMPARE TO CREST®PRO-HEALTH®INTENSE CLEAN MINT MOUTHWASH*

TopCare® everyday

Powerful Fresh

Antigingivitis/Antiplaque

Mouthwash

FRESH MINT

- Kills 99% of many bad breath germs**
- Freshens your breath
- Helps prevent plaque and gingivitis

IMPORTANT: Read directions for proper use.

1 L (1.05 QT) 33.8 FL OZ